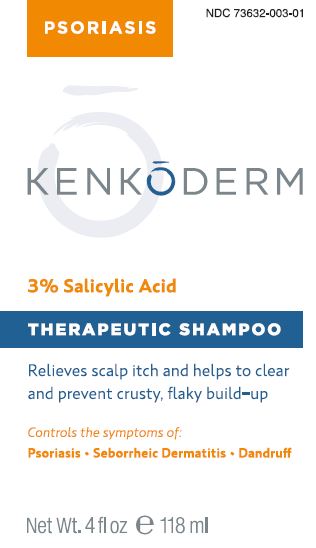 DRUG LABEL: Kenkoderm Psoriasis
NDC: 73632-003 | Form: SHAMPOO
Manufacturer: Olympus Trading Company, LLC
Category: otc | Type: HUMAN OTC DRUG LABEL
Date: 20260109

ACTIVE INGREDIENTS: SALICYLIC ACID 3 g/100 mL
INACTIVE INGREDIENTS: WATER; SODIUM C14-16 OLEFIN SULFONATE; TRIETHANOLAMINE LAURYL SULFATE; COCAMIDOPROPYL HYDROXYSULTAINE; EDETATE DISODIUM ANHYDROUS; SODIUM HYDROXIDE

Kenkoderm Psoriasis Shampoo

Active Ingredient

Salicylic Acid 3.0%

Purpose

Anti-psoriasis, Anti-dandruff, Anti-seborrheic dermatitis

Use

Control the symptoms of dandruff, itching and build-up associated with Psoriasis and Seborrheic Dermatitis.

Warnings

For external use only

Ask a doctor before use if you have:

- A condition that covers a large area of the body
- Allergy or sensitivity to Salicylic Acid

When using this product

do not get into eyes. If contact occurs, rinse eyes thoroughly with water.

Stop use and ask a doctor if

condition worsens or does not improve after regular use of this product as directed.

Keep out of reach of children.

If swallowed, get medical help or contact Poison Control Center right away.

Directions

- Wet hair thoroughly
- Apply a liberal amount of shampoo and massage into lather
- Allow lather to remain on scalp for several minutes
- Rinse hair well and repeat
- For best results use at least twice a week or as directed by a doctor

Other information

Store away from direct sunlight

Inactive ingredients

Water (Aqua), Sodium C14-16 Olefin Sulfonate, TEA Lauryl Sulfate, Cocamidopropyl Betaine, PEG-8 Distearate, Cocamidopropyl Hydroxysultaine, Disodium EDTA, Sodium Hydroxide.

Questions or comments?

Call 1-703-829-7627

Principal Display Panel

PSORIASIS NDC 73632-003-01
KENKŌDERM
3% Salicylic Acid
THERAPEUTIC SHAMPOO
Relieves scalp itch and helps to clear
and prevent crusty, flaky build-up
Controls the symptoms of:
Psoriasis · Seborrheic Dermatitis · Dandruff
Net Wt. 4 fl oz ℮118 ml
Kenkōderm, Arlington, VA 22201 · ©2020 All rights reserved · kenkoderm.com

Label